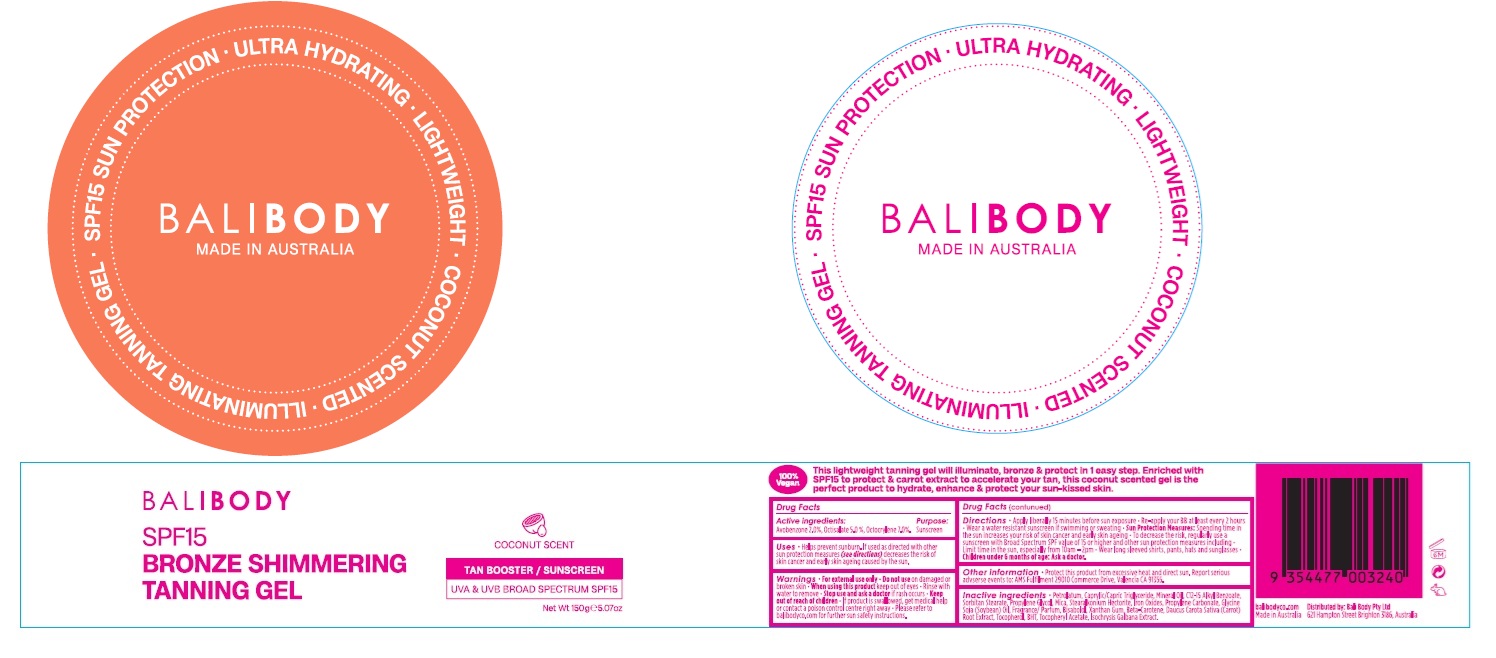 DRUG LABEL: BALI BODY SPF15 BRONZE SHIMMERING TANNING
NDC: 70630-0038 | Form: GEL
Manufacturer: Bali Body Pty Ltd
Category: otc | Type: HUMAN OTC DRUG LABEL
Date: 20250616

ACTIVE INGREDIENTS: OCTOCRYLENE 70 mg/1 g; OCTISALATE 50 mg/1 g; AVOBENZONE 20 mg/1 g
INACTIVE INGREDIENTS: ISOCHRYSIS GALBANA WHOLE; BETA CAROTENE; TOCOPHEROL; .ALPHA.-TOCOPHEROL ACETATE, DL-; SORBITAN MONOSTEARATE; BUTYLATED HYDROXYTOLUENE; XANTHAN GUM; STEARALKONIUM HECTORITE; SOYBEAN OIL; MICA; PROPYLENE CARBONATE; LEVOMENOL; PROPYLENE GLYCOL; CARROT; PETROLATUM; MEDIUM-CHAIN TRIGLYCERIDES; MINERAL OIL; ALKYL (C12-15) BENZOATE

BALI BODY SPF15 BRONZE SHIMMERING TANNING GEL

Active ingredients:

Avobenzone 2.0%

Octisalate 5.0%

Octocrylene 7.0%

Purpose

Sunscreen

Uses

- Helps prevent sunburn. If used as directed with other sun protection measures (see directions) decreases the risk of skin cancer and early skin ageing caused by the sun.

Warnings

- For external use only

Do not use

on damaged or broken skin

When using this product

keep out of eyes. Rinse with water to remove.

Stop use and ask a doctor

if rash occurs

Keep out of reach of children.

If product is swallowed, get medical help or contact a poison control centre right away. Please refer to balibody.com for further sun safety instructions.

Directions

- Apply liberally 15 minutes before sun exposure.
- Re-apply your BB at least every 2 hours
- Wear a water resistant sunscreen if swimming or sweating
- Sun Protection Measures: Spending time in the sun increases your risk of skin cancer and early skin ageing.
- To decrease the risk, regularly use a sunscreen with Broad Spectrum SPF value of 15 or higher and other sun protection measures including
- Limit time in the sun, especially from 10am - 2pm.
- Wear long sleeved shirts, pants, hats and sunglasses
- Children under 6 months of age: Ask a doctor.

Other information

- Protect this product from excessive heat and direct sun. Report serious adverse events to: AMS Fulfillment 29010 Commerce Drive, Valencia CA 91355

Inactive ingredients

Petrolatum, Caprylic/Capric Triglyceride, Mineral Oil, C12-15 Alkyl Benzoate, Sorbitan Stearate, Propylene Glycol, Mica, Stearalkonium Hectorite, Iron Oxides, Propylene Carbonate, Glycine Soja (Soybean) Oil, Fragrance/Parfum, Bisabolol, Xanthan Gum, Beta-Carotene, Daucus Carota Sativa (Carrot) Root Extract, Tocopherol, BHT, Tocopheryl Acetate, Isochrysis Galbana Extract.